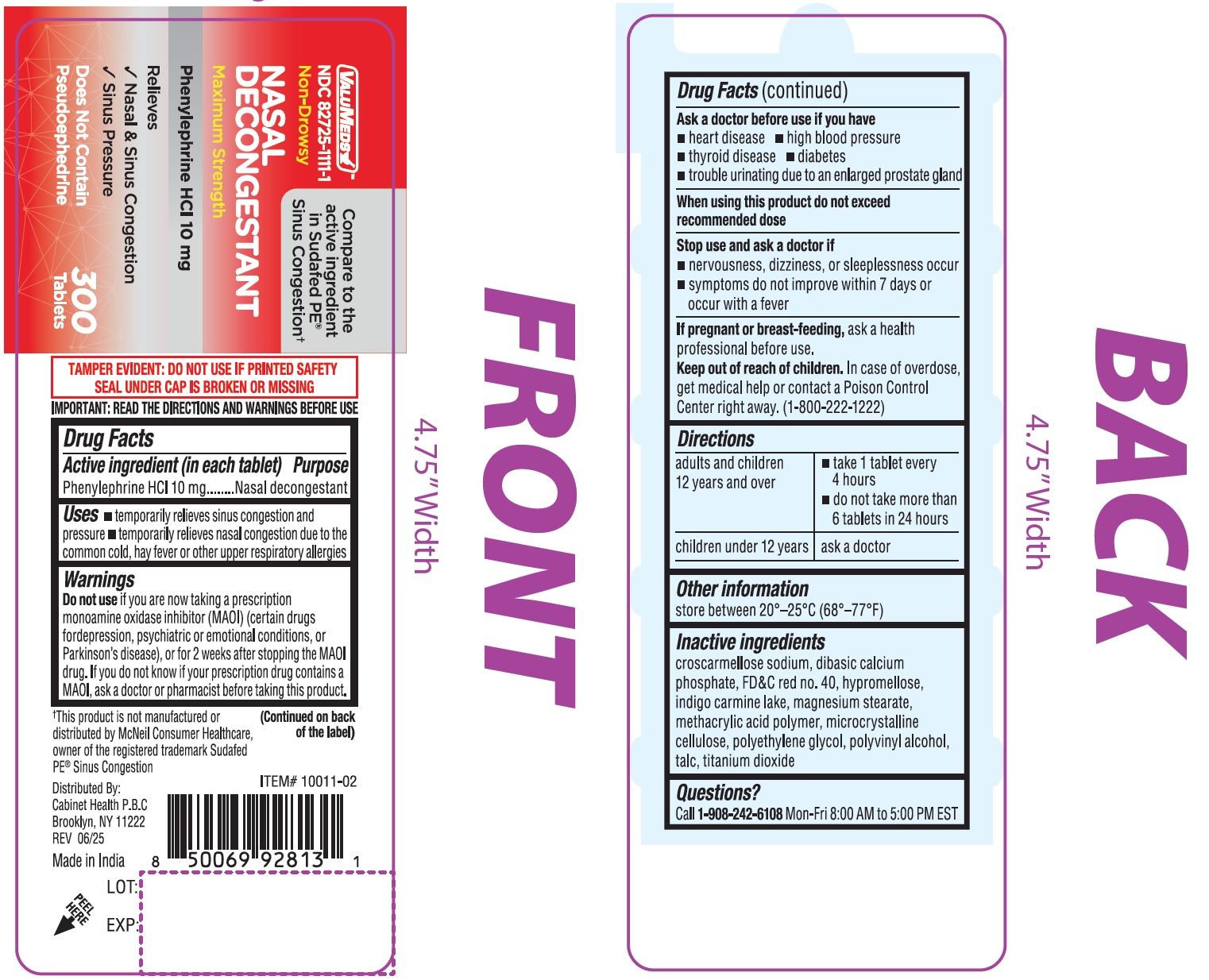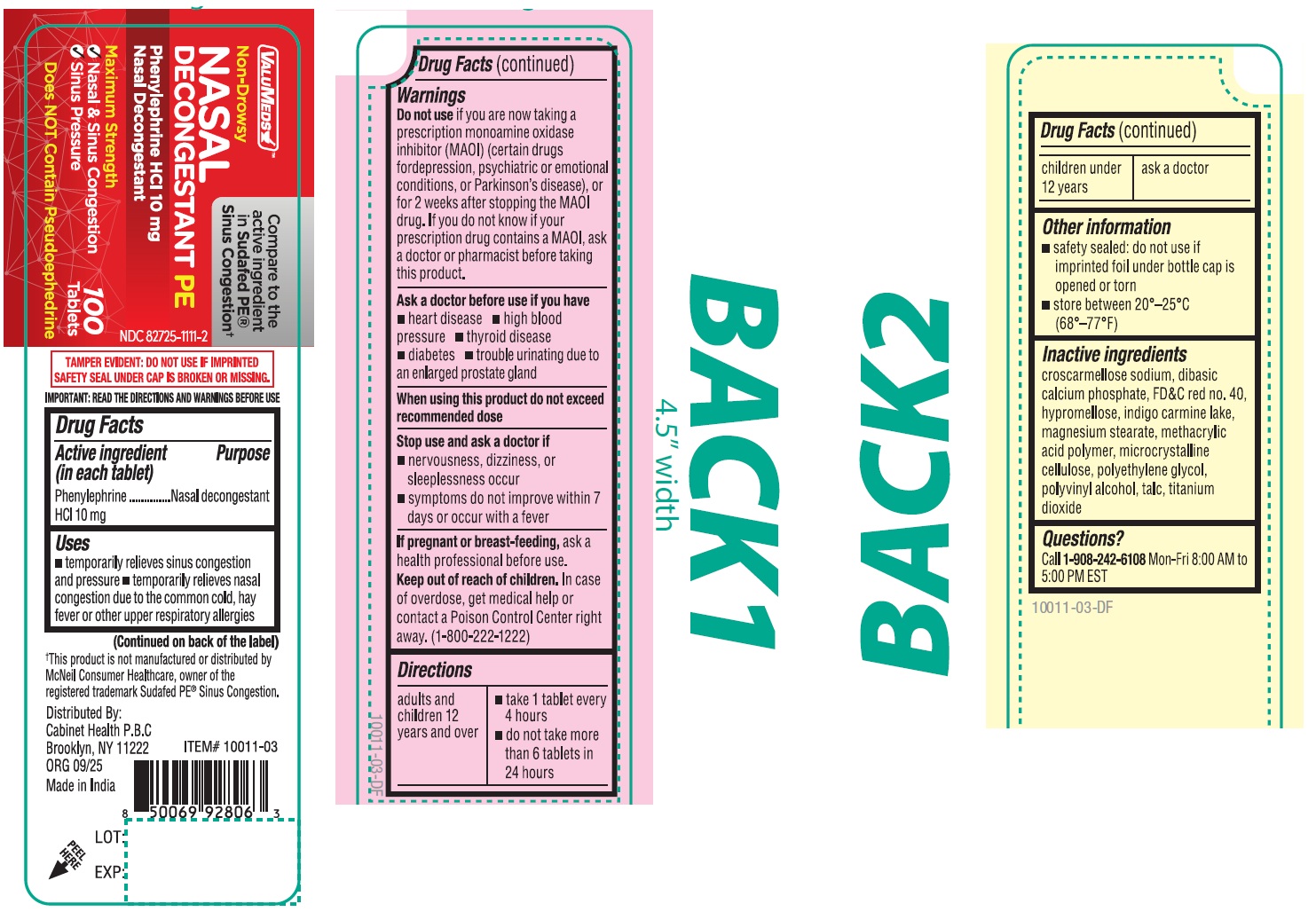 DRUG LABEL: ValuMeds Nasal Decongestant Phenylephrine HCl
NDC: 82725-1111 | Form: TABLET
Manufacturer: Cabinet Health P.B.C.
Category: otc | Type: HUMAN OTC DRUG LABEL
Date: 20251106

ACTIVE INGREDIENTS: PHENYLEPHRINE HYDROCHLORIDE 10 mg/1 1
INACTIVE INGREDIENTS: CROSCARMELLOSE SODIUM; ANHYDROUS DIBASIC CALCIUM PHOSPHATE; FD&C RED NO. 40; HYPROMELLOSE, UNSPECIFIED; MAGNESIUM STEARATE; MICROCRYSTALLINE CELLULOSE; POLYETHYLENE GLYCOL, UNSPECIFIED; POLYVINYL ALCOHOL, UNSPECIFIED; TALC; TITANIUM DIOXIDE

ValuMeds Nasal Decongestant, Phenylephrine HCl

Active Ingredient (in each tablet)

Phenylephrine HCl 10 mg

Purpose

Nasal decongestant

Uses

• temporarily relieves sinus congestion and pressure •temporarily relieves nasal congestion due to the common cold, hay fever or other upper respiratory allergies

Warnings

Do not use

if you are now taking a prescription monoamine oxidase inhibitor (MAOI) (certain drugs fordepression, psychiatric or emotional conditions, or Parkinson's disease), or for 2 weeks after stopping the MAOI drug. If you do not know if your prescription drug contains a MAOI, ask a doctor or pharmacist before taking this product.

Ask a doctor before use if you have

• heart disease • high blood pressure • thyroid disease • diabetes • trouble urinating due to an enlarged prostate gland

When using this product

do not exceed recommended dose

Stop use and ask a doctor if

- nervousness, dizziness, or sleeplessness occur
- symptoms do not improve within 7 days or occur with a fever

If pregnant or breast-feeding,

ask a health professional before use.

Keep out of reach of children.

In case of overdose, get medical help or contact a Poison Control Center right away. (1-800-222-1222)

Directions

adults and children 12 years and over | - take 1 tablet every 4 hours - do not take more than 6 tablets in 24 hours
children under 12 years | ask a doctor

Other information

store between 20°–25°C (68°–77°F)

Inactive ingredients

croscarmellose sodium, dibasic calcium phosphate, FD&C red no. 40, hypromellose, indigo carmine lake, magnesium stearate, methacrylic acid polymer, microcrystalline cellulose, polyethylene glycol, polyvinyl alcohol, talc, titanium dioxide

Questions or comments?

Call 1-908-242-6108Mon-Fri 8:00 AM to 5:00PM EST